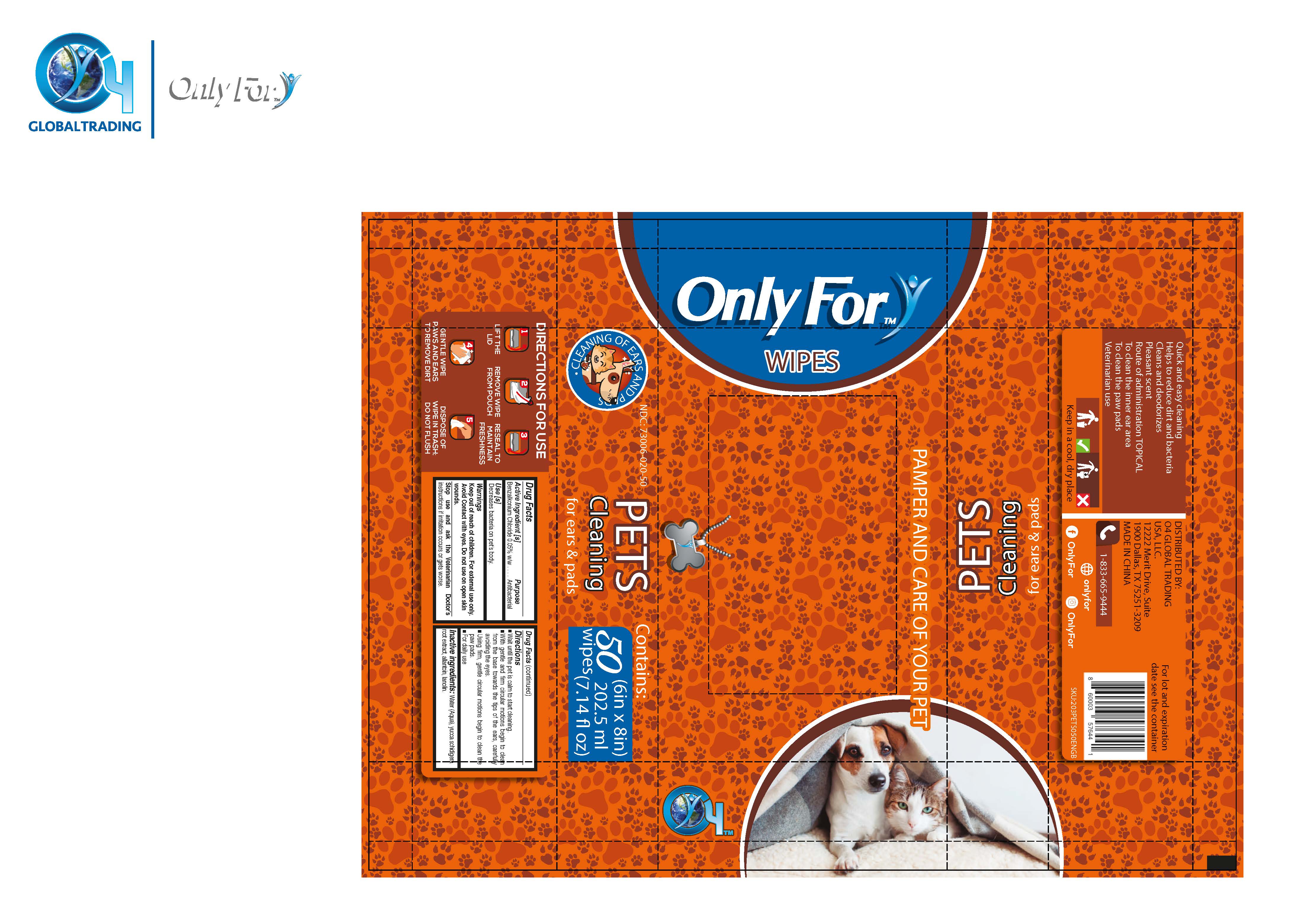 DRUG LABEL: ONLY FOR
NDC: 73006-020 | Form: CLOTH
Manufacturer: O4 Global Trading USA LLC
Category: animal | Type: OTC ANIMAL DRUG LABEL
Date: 20210312

ACTIVE INGREDIENTS: BENZALKONIUM CHLORIDE 0.05 g/100 g
INACTIVE INGREDIENTS: LANOLIN 0.05 g/100 g; WATER 99.55 g/100 g; PEG-70 LANOLIN 0.05 g/100 g; ALLANTOIN 0.05 g/100 g; YUCCA SCHIDIGERA ROOT 0.3 g/100 g

ANTIBACTERIAL WIPES- benzalkonium chloride cloth (50 WIPES)

Use

Decreases bacteria on pet’s body.

Active Ingredients

Benzalkonium chloride 0.05% w/w. Purpose: Antiseptic

Purpose

Antiseptic/Antibacterial

Directions

1. Wait until the pet is calm to start cleaning

2. With gentle and firm circular motions begin to clean from the base towards the tips of the ears, carefully avoiding the eyes

3. Using firm, gentle circular motions begin to clean the paw pads.

4. For daily use

Keep out of reach of children

Warnings & Precautions

Keep out of reach of children. For external use only. Avoid Contact with eyes. Do not use on open skin wounds.

Storage and Handling

Keep in a cool and dry place.

LIFT TH LID

REMOVE WIPE FROM POUCH

RESEAL TO MAINTAIN FRESHNESS

GENTLE WIPE PAWS AND EARS TO REMOVE DIRT

DISPOSE OF WIPE IN TRASH; DO NOT FLUSH

Inactive Ingredients

Water (Aqua), yucca schidigera root extract, allantoin, lanolin.

Stop use

Stop use and ask the Veterinarian Doctor’s instructions if irritation occurs or gets worse.

Package Label

NDC: 73006-020-50